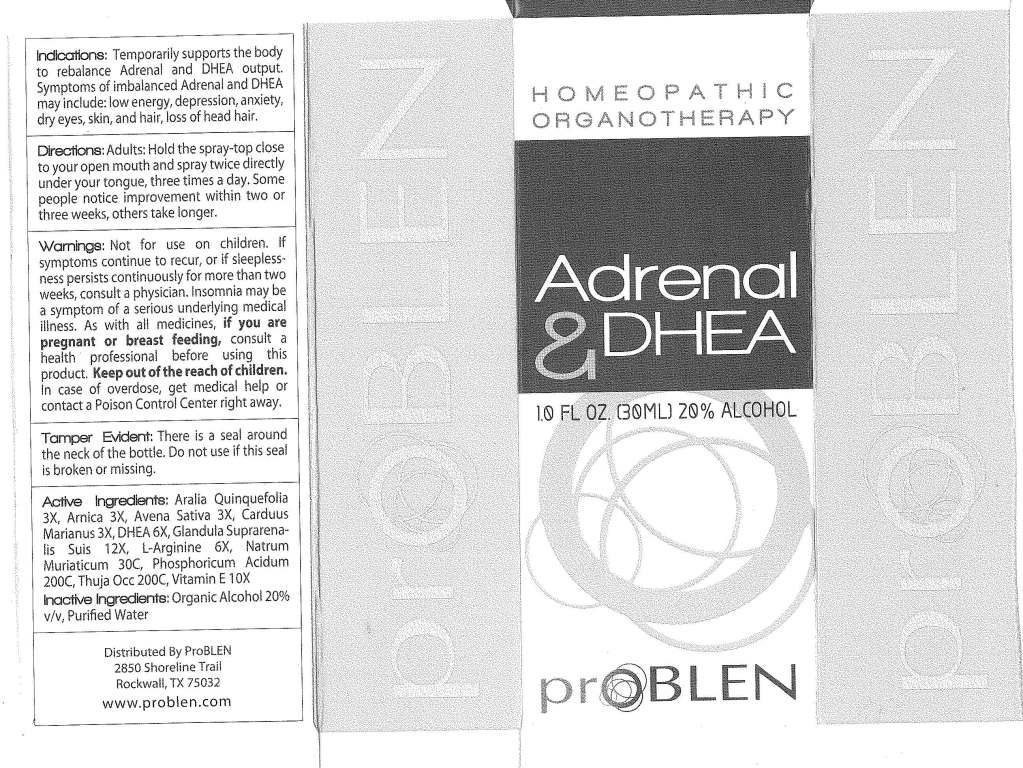 DRUG LABEL: Adrenal and DHEA
NDC: 50845-0086 | Form: SPRAY
Manufacturer: Liddell Laboratories, Inc.
Category: homeopathic | Type: HUMAN OTC DRUG LABEL
Date: 20101220

ACTIVE INGREDIENTS: AMERICAN GINSENG 3 [hp_X]/1 mL; ARNICA MONTANA 3 [hp_X]/1 mL; AVENA SATIVA FLOWERING TOP 3 [hp_X]/1 mL; SILYBUM MARIANUM SEED 3 [hp_X]/1 mL; PRASTERONE 6 [hp_X]/1 mL; SUS SCROFA ADRENAL GLAND 12 [hp_X]/1 mL; ARGININE 6 [hp_X]/1 mL; SODIUM CHLORIDE 30 [hp_C]/1 mL; PHOSPHORIC ACID 200 [hp_C]/1 mL; THUJA OCCIDENTALIS LEAFY TWIG 200 [hp_C]/1 mL; ALPHA-TOCOPHEROL 10 [hp_X]/1 mL
INACTIVE INGREDIENTS: WATER; ALCOHOL

Adrenal and DHEA

ACTIVE INGREDIENT

ACTIVE INGREDIENTS: Aralia quinquefolia 3X, Arnica montana 3X, Avena sativa 3X, Carduus marianus 3X, DHEA 6X, Glandula suprarenalis suis 12X, L-arginine 6X, Natrum muriaticum 30C, Phosphoricum acidum 200C, Thuja occidentalis 200C, Vitamin E 10X.

PURPOSE

INDICATIONS: Temporarily supports the body to rebalance Adrenal and DHEA output. Symptoms of imbalanced Adrenal and DHEA may include: low energy, depression, anxiety, dry eyes, skin, and hair, loss of head hair.

WARNINGS

WARNINGS: Nor for use on children. If symptoms continue to recur, or if sleeplessness persists continuously for more than two weeks, consult a physician. Insomnia may be a symptom of a serious underlying medical illness.

As with all medicines, if you are pregnant or breast feeding, consult a health professional before using this product.

Keep out of reach of children. In case of overdose, get medical help or contact a Poison Control Center right away.

TAMPER EVIDENT: There is a seal around the neck of the bottle. Do not use if this seal is broken or missing.

DOSAGE AND ADMINISTRATION

DIRECTIONS: Adults: hold the spray-top close to your open mouth and spray twice directly under your tongue, three times a day. Some people notice improvement within two or three weeks, others take longer.

INACTIVE INGREDIENT

INACTIVE INGREDIENTS: Organic alcohol 20% v/v, Purified water.

KEEP OUT OF REACH OF CHILDREN. In case of overdose, get medical help or contact a Poison Control Center right away.

INDICATIONS AND USAGE

INDICATIONS: Temporarily supports the body to rebalance Adrenal and DHEA output. Symptoms of imbalanced Adrenal and DHEA may include: low energy, depression, anxiety, dry eyes, skin, and hair, loss of head hair.

QUESTIONS

Distributed By ProBLEN

2850 Shoreline Trail

Rockwall, TX 75032

www.problen.com

PACKAGE LABEL

HOMEOPATHIC

ORGANOTHERAPY

Adrenal and DHEA

proBLEN

1 FL OZ (30 ML)